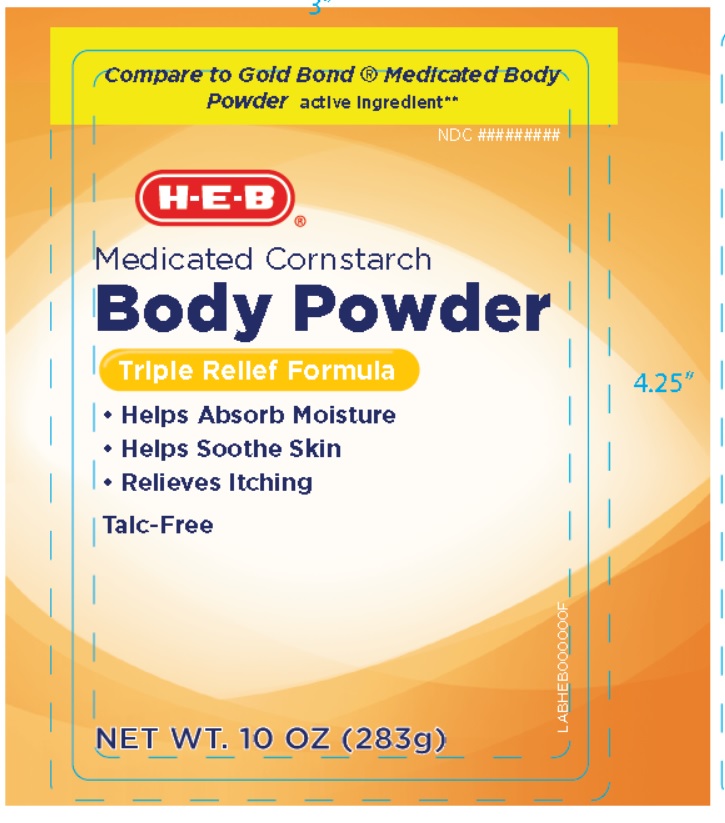 DRUG LABEL: HEB Medicated Cornstarch Body Powder
NDC: 42669-217 | Form: POWDER
Manufacturer: Davion, Inc
Category: otc | Type: HUMAN OTC DRUG LABEL
Date: 20251229

ACTIVE INGREDIENTS: MENTHOL 0.15 g/100 g
INACTIVE INGREDIENTS: STARCH, CORN; TRICALCIUM PHOSPHATE; SODIUM BICARBONATE; ZINC OXIDE; SALICYLIC ACID; ZINC STEARATE; EUCALYPTUS OIL; PEPPERMINT OIL

H-E-B Medicated Cornstarch Body Powder Triple Relief Formula

Active Ingredient

Menthol 0.15%

Purpose

External Analgesic

Uses

Temporary relief of pain and itch associate with:

- Minor Cuts
- Sunburn
- Insect Bites
- Scrapes
- Minor Burns
- Minor Skin Irritations

Warning

- For external use only
- Avoid contact with eyes

Stop use and ask a doctor if

- condition worsens
- symptoms persist for more than 7 days or clear up and occur again within few days

Keep out of reach of children

In case of accidental ingestion, get medical help or contact a Poison Control Center right away.

Directions

- Adults and children 2 years and older - Apply freely upto 3 or 4 times daily
- Children under 2 years - Ask a doctor
- For best results, dry skin throughly before applying

Inactive Ingredients

Zea Mays (Corn) Starch, Tricalcium Phosphate, Sodium Bicarbonate, Zinc Oxide, Salicylic Acid, Zinc Stearate, Eucalyptus Oil, Peppermint Oil.

PRINCIPAL DISPLAY PANEL

NDC 42669-217-10

Compare to Gold Bond ® Medicated Body Powder active ingredient**

H-E-B Medicated Cornstarch Body Powder

TRIPLE RELIEF FORMULA

- Helps Absorbs Moisture
- Helps Soothe Skin
- Relieves Itching

Talc-Free

Net wt 10oz (283 g)